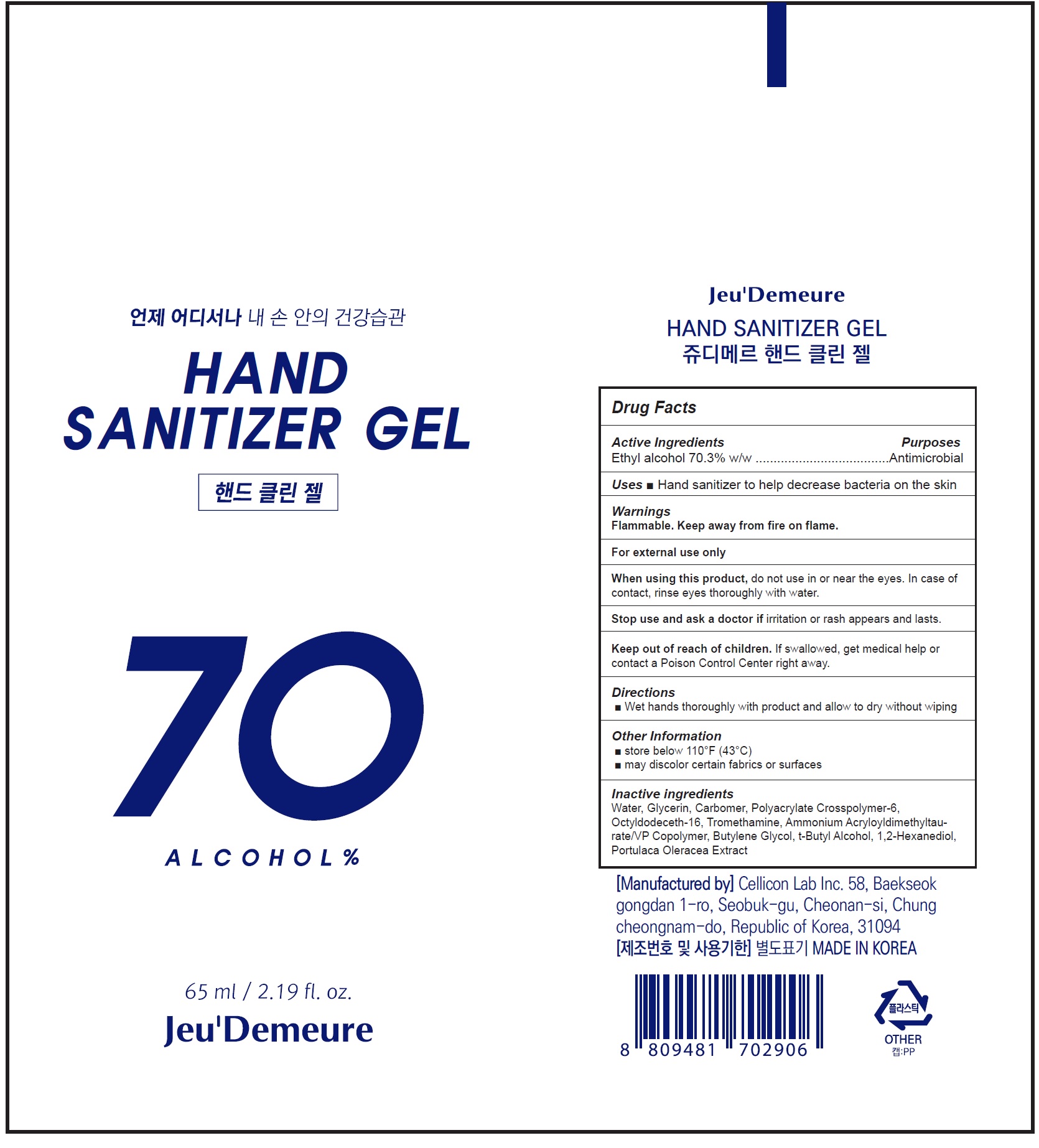 DRUG LABEL: HAND SANITIZER gel
NDC: 81601-001 | Form: GEL
Manufacturer: Cellicon Lab Inc.
Category: otc | Type: HUMAN OTC DRUG LABEL
Date: 20210402

ACTIVE INGREDIENTS: ALCOHOL 0.703 mL/1 mL
INACTIVE INGREDIENTS: WATER; GLYCERIN; CARBOMER HOMOPOLYMER, UNSPECIFIED TYPE; AMMONIUM ACRYLOYLDIMETHYLTAURATE, DIMETHYLACRYLAMIDE, LAURYL METHACRYLATE AND LAURETH-4 METHACRYLATE COPOLYMER, TRIMETHYLOLPROPANE TRIACRYLATE CROSSLINKED (45000 MPA.S); OCTYLDODECETH-16; TROLAMINE; AMMONIUM ACRYLOYLDIMETHYLTAURATE/VP COPOLYMER; BUTYLENE GLYCOL; TERT-BUTYL ALCOHOL; 1,2-HEXANEDIOL; PURSLANE

81601-001_HAND SANITIZER GEL

Active ingredient

Ethyl alcohol 70.3% w/w

Purpose

Antimicrobial

Use

- Hand sanitizer to help decrease bacteria on the skin

Warnings

Flammable. Keep away from fire or flame.

For external use only

When using this product do not use in or near the eyes. In case of contact, rinse eyes thoroughly with water.

Stop use and ask a doctor if irritation or rash appears and lasts

Keep out of reach of children. If swallowed, get medical help or contact a Poison Control Center right away.

Directions

- Put enough product in your palm to cover hands and rub hands together briskly until dry.
- Children under 6 years of age should be supervised when using the product

Other information

- Store below 110°F (43°C)
- May discolor certain fabrics or surfaces

Inactive ingredients

Water, Glycerin, Carbomer, Polyacrylate Crosspolymer-6, Octyldodeceth-16, Tromethamine, Ammonium Acryloyldimethyltaurate/VP Copolymer, Butylene Glycol, t-Butyl Alcohol, 1,2-Hexanediol, Portulaca Oleracea Extract